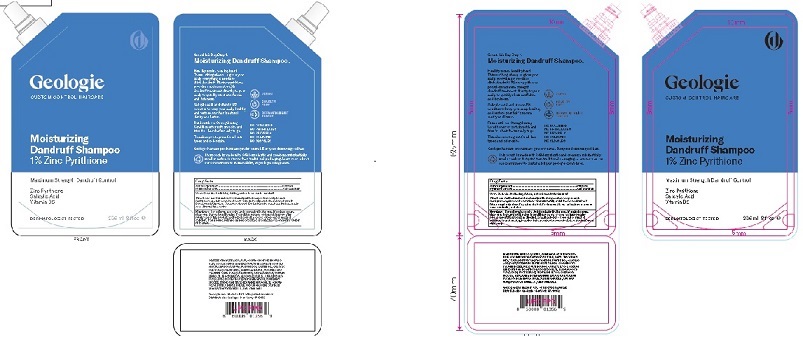 DRUG LABEL: MOISTURIZING DANDRUFF

NDC: 54111-169 | Form: SHAMPOO
Manufacturer: Bentley Laboratories, LLC
Category: otc | Type: HUMAN OTC DRUG LABEL
Date: 20251215

ACTIVE INGREDIENTS: PYRITHIONE ZINC 1 g/100 mL
INACTIVE INGREDIENTS: WATER; SODIUM C14-16 OLEFIN SULFONATE; COCAMIDOPROPYL HYDROXYSULTAINE; LUVISET 360; PROPANEDIOL; PANTHENOL; SALICYLIC ACID; POLYQUATERNIUM-53; PHENOXYETHANOL; COCAMIDOPROPYLAMINE OXIDE; POLYQUATERNIUM-6 (15000 MW); CAPRYLYL GLYCOL; SODIUM BENZOATE; PEG-120 METHYL GLUCOSE DIOLEATE; RADISH; PROPYLENE GLYCOL; SODIUM HYDROXIDE; TRISODIUM ETHYLENEDIAMINE DISUCCINATE; SODIUM METHYLENEBISNAPHTHALENESULFONATE; SODIUM CHLORIDE; XANTHAN GUM; HYDROXYCITRONELLAL; .ALPHA.-AMYLCINNAMALDEHYDE

Geologie Moisturizing Dandruff Shampoo 1% Pyrithione Zinc

DRUG FACTS

Active Ingredient ........... Pyrithione Zinc 1%

Purpose .........Anti-Dandruff

INDICATIONS AND USAGE

Uses: Controls skin itching, and redness due to dandruff.

DOSAGE AND ADMINISTRATION

Directions:Get hair wet and coat evenly with shampoo from scalp to ends.
Gently massage into scalp for at least 1 minute to fully exfoliate and moisturize it.
Rinse completely clean. Repeat as desired. For best results use at least twice a week
or as directed by a doctor.

WARNINGS

Warnings: For external use only. Avoid contact with eyes. If contact occurs, rinse
Eyes thoroughly with water. If condition worsens or does not improve after regular use
of this product as directed, consult a doctor.

Keep out of reach of children

If swallowed, get medical help or contact or contact a Poison Control Center
right away.

INACTIVE INGREDIENT

INGREDIENTS: WATER/AQUA/EAU, SODIUM C14-16 OLEFIN SULFONATE, COCAMIDOPROPYL HYDROXYSULTAINE, ACRYLATES COPOLYMER, FRANGRANCE/PARFUM, PROPANEDIOL, PANTHENOL, SALICYLIC ACID, POLYQUATERNIUM-53, PHENOXYETHANOL, COCAMIDOPROPYLAMINE OXIDE, POLYQUATERNIUM-6, CAPRYLYL GLYCOL, SODIUM BENZOATE, PEG-120 METHYL GLUCOSE DIOLEATE, RAPHANUS SATIVUS (RADISH) ROOT EXTRACT, PROPYLENE GLYCOL, SODIUM HYDROXIDE, TRISODIUM ETHYLENEDIAMINE DISUCCINATE, SODIUM POLYNAPHTHALENESULFONATE, SODIUM CHLORIDE, XANTHAN GUM, HYDROXYCITRONELLAL, AMYL CINNAMAL

Geologie Package

Geologie

CUSTOM CONTROL HAIRCARE

Moisturizing

Dandruff Shampoo

1% Zinc Pyrithione

236 ml 8 fl oz
Geologie.com Made in USA of imported materials
Distributed by Geologie New York, NY 10163

res